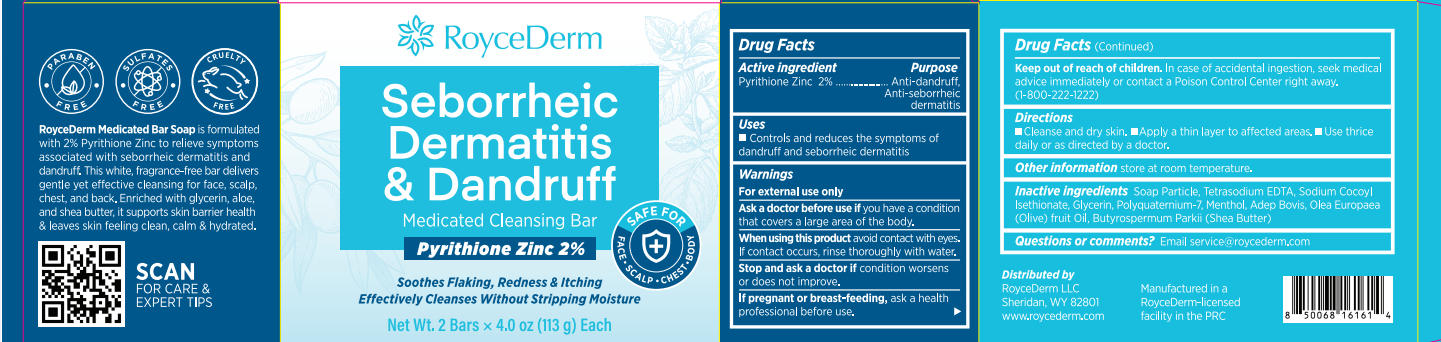 DRUG LABEL: RoyceDerm Seborrheic Dermatitis and Dandruff Medicated Cleansing Bar
NDC: 85424-008 | Form: SOAP
Manufacturer: RoyceDerm LLC
Category: otc | Type: HUMAN OTC DRUG LABEL
Date: 20250805

ACTIVE INGREDIENTS: PYRITHIONE ZINC 4.52 g/226 g
INACTIVE INGREDIENTS: BUTYROSPERMUM PARKII (SHEA) BUTTER; GLYCERIN; SODIUM COCOYL ISETHIONATE; POLYQUATERNIUM-7; MENTHOL; TETRASODIUM EDTA; ADEPS BOVIS; OLEA EUROPAEA (OLIVE) FRUIT OIL

Initial Drug Listing - RoyceDerm Seborrheic Dermatitis & Dandruff Medicated Cleansing Bar

ACTIVE INGREDIENT

Pyrithione Zinc 2%

PURPOSE

- Anti-dandruff
- Anti-seborrheic dermatitis

DOSAGE AND ADMINISTRATION

Controls and reduces the symptoms of dandruff and seborrheic dermatitis

WARNINGS

For external use only

ASK DOCTOR

you have a conditionthat covers a large area of the body.

WHEN USING

avoid contact with eyesIf contact occurs, rinse thoroughly with water.

STOP USE

if condition worsensor does not improve.

PREGNANCY OR BREAST FEEDING

ask a healthprofessional before use.

KEEP OUT OF REACH OF CHILDREN

In case of accidental ingestion, seek medical advice immediately or contact a Poison Control Center right away.(1-800-222-1222)

INDICATIONS AND USAGE

- Cleanse and dry skin.
- Apply a thin layer to affected areas.
- Use thricedaily or as directed by a doctor.

OTHER SAFETY INFORMATION

store at room temperature.

INACTIVE INGREDIENT

Tetrasodium EDTA, Sodium Cocoyl Isethionate, Glycerin, Polyquaternium-7, Menthol, Adep Bovis, Olea Europaea(Olive) fruit Oil, Butyrospermum Parkii (Shea Butter)

QUESTIONS

Email service@roycederm.com